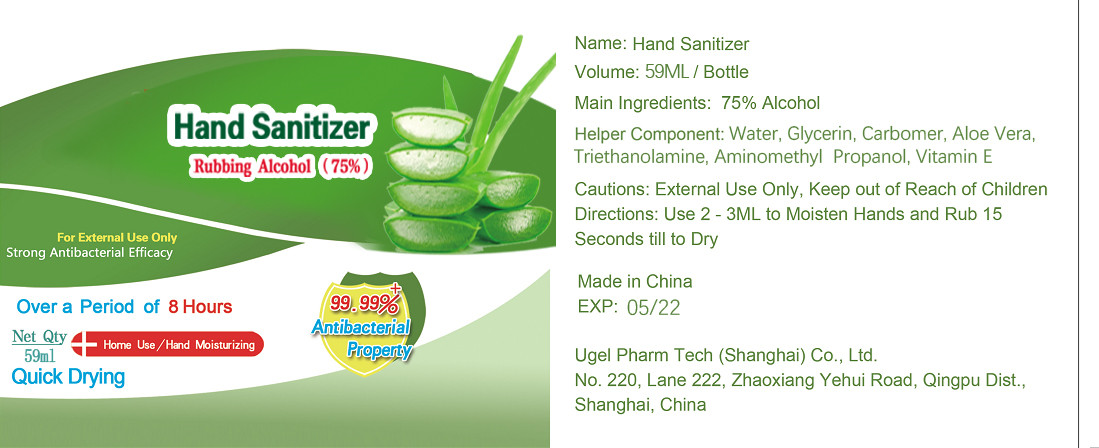 DRUG LABEL: Hand Sanitizer
NDC: 55262-003 | Form: GEL
Manufacturer: Ugel Pharm Tech (Shanghai) Co., Ltd.
Category: otc | Type: HUMAN OTC DRUG LABEL
Date: 20200609

ACTIVE INGREDIENTS: ALCOHOL 44.25 mL/59 mL
INACTIVE INGREDIENTS: TROLAMINE; WATER; GLYCERIN; ALOE; AMINOMETHYLPROPANOL; CARBOMER HOMOPOLYMER, UNSPECIFIED TYPE; .ALPHA.-TOCOPHEROL

DOSAGE AND ADMINISTRATION

Store in a cool and dry place

INACTIVE INGREDIENT

Water, Glycerin, Carbomer, Aloe Vera, Triethanolamine, Aminomethyl Propanol, Vitamin E

INDICATIONS AND USAGE

Use 2 - 3ML to Moisten Hands and Rub 15 Seconds till to Dry

ACTIVE INGREDIENT

Alcohol 75%

keep out of reach of children

PURPOSE

Disinfection
Sterilization
No Rinseing

WARNINGS

External Use Only, Keep out of Reach of Children